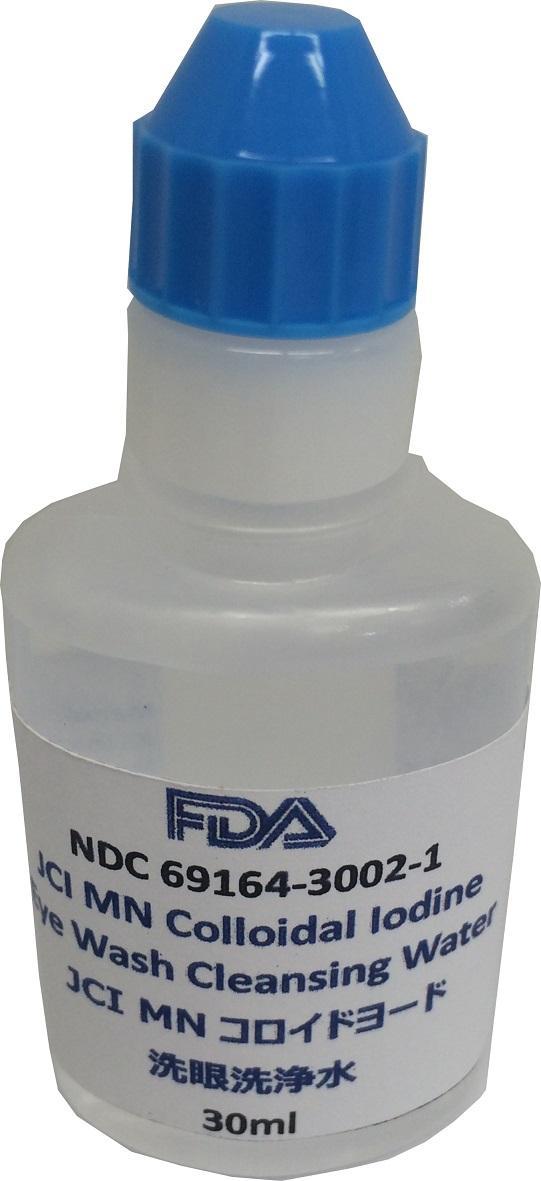 DRUG LABEL: JCI MN Colloidal Iodine Eye Wash Cleansing Water (Quasi Drug)
NDC: 69164-3002 | Form: SOLUTION
Manufacturer: JCI INSTITUTE OF MEDICAL SCIENCE
Category: otc | Type: HUMAN OTC DRUG LABEL
Date: 20180511

ACTIVE INGREDIENTS: IODINE 0.1 g/100 mL
INACTIVE INGREDIENTS: WATER

Drug Facts

ACTIVE INGREDIENT

sodium iodide

INACTIVE INGREDIENT

electrolytic-reduction water

PURPOSE

opthalmic disorders
intranasal lesion, intra-oral lesion
prevention of the diseases above mentioned

keep out of reach of the children

INDICATIONS AND USAGE

apply eyewash several times a day in case of ophthalmic disorders
adjust the mumber of times being applying the eye drop, depending on symptho
it is better to increase the number of times for the quick recovery
for the intranasal disease, it is recommended to apply the drops several times a day
for the intra-oral disease, keep the drop in the mouth or use as toothpaste

WARNINGS

there may occurs the case of irritability when applying eye drop or nasal drop
do not worry about it because it is caused by the reaction of Iodine
But is it possibly think of the susceptibility to Iodine, which seldom occurs.
in case of irritability or rash, stop the use immediately and discuss with doctors
keep out of the direct sunlight

DOSAGE AND ADMINISTRATION

ophthalmic and intranasal use